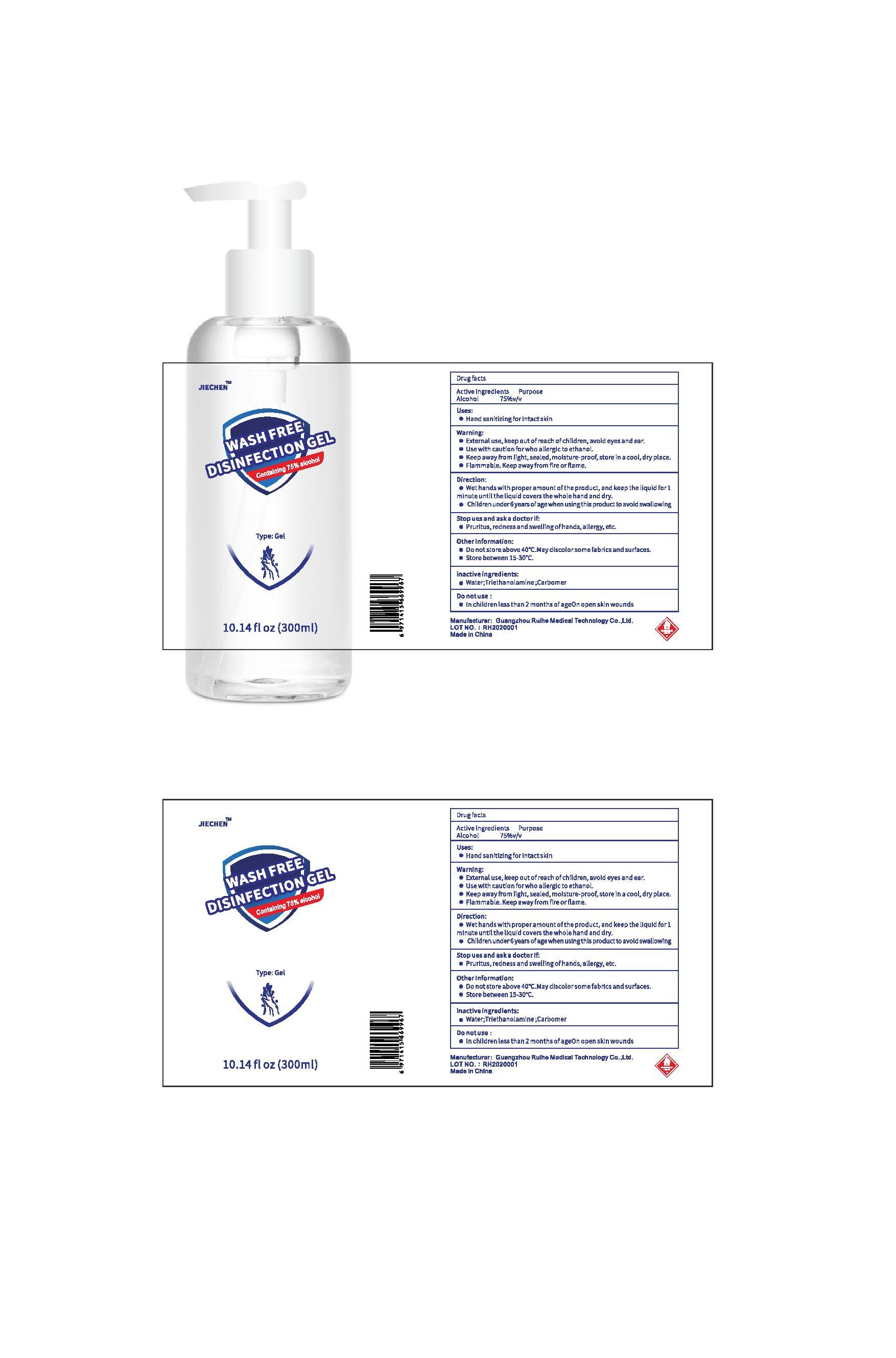 DRUG LABEL: Wash Free Disinfection Gel
NDC: 74180-001 | Form: GEL
Manufacturer: Guangzhou Ruihe Medical Technology Co.,Ltd.
Category: otc | Type: HUMAN OTC DRUG LABEL
Date: 20200407

ACTIVE INGREDIENTS: ALCOHOL 75 mL/100 mL
INACTIVE INGREDIENTS: TROLAMINE; CARBOMER HOMOPOLYMER, UNSPECIFIED TYPE; WATER

Active Ingredient(s)

Alcohol 75% v/v

Purpose

Antiseptic

Use

Hand sanitizing for intact skin

Warnings

- External use, keep out of reach of children, avoid eyes and ear.
- Use with caution for who allergic to ethanol.
- Keep away from light, sealed, moisture-prood, store in a cool, dry place.
- Flammable. Keep away from fire or flame

Do not use

- in children less than 2 months of age
- on open skin wounds

STOP USE

Pruritus, redness, and swelling of hands, allergy, etc.

Keep out of reach of children.

Directions

- Wet hand with proper amount of the product, and keep the liquid for 1 minute until the liquid covers the whole hand and dry.
- Children under 6 years of age when using this product to avoid swallowing.

Other information

- Do not store above 40C. May discolor some fabrics and surfaces.
- Store between 15-30C

Inactive ingredients

Water, Triethanolamine, Carbomer